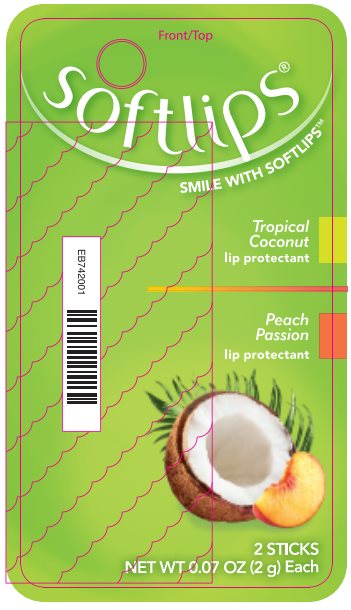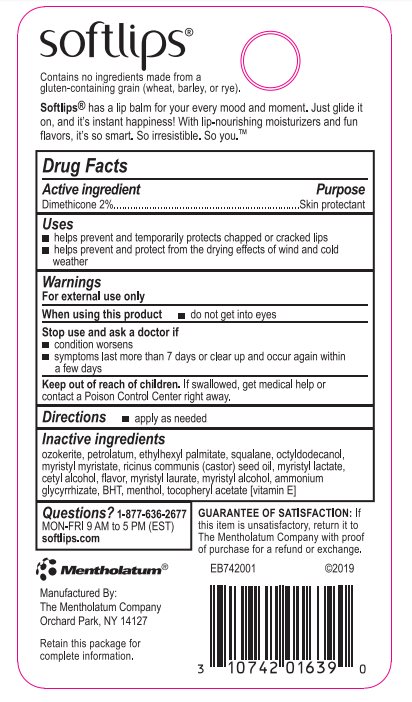 DRUG LABEL: Softlips
NDC: 10742-7005 | Form: STICK
Manufacturer: The Mentholatum Company
Category: otc | Type: HUMAN OTC DRUG LABEL
Date: 20241217

ACTIVE INGREDIENTS: DIMETHICONE 20 mg/1 g
INACTIVE INGREDIENTS: CERESIN; PETROLATUM; ETHYLHEXYL PALMITATE; SQUALANE; OCTYLDODECANOL; MYRISTYL MYRISTATE; CASTOR OIL; MYRISTYL LACTATE; CETYL ALCOHOL; MYRISTYL LAURATE; MYRISTYL ALCOHOL; AMMONIUM GLYCYRRHIZATE; BUTYLATED HYDROXYTOLUENE; LEVOMENTHOL; .ALPHA.-TOCOPHEROL ACETATE

Drug Facts

Active ingredients

Dimethicone 2%

Purpose

Dimethicone - Skin protectant

Uses

- helps prevent and temporarily protects chapped or cracked lips
- helps prevent and protect from the drying effects of wind and cold weather

Warnings

For external use only

When using this product

- do not get into eyes

Stop use and ask a doctor if

- condition worsens
- symptoms last more than 7 days or clear up and occur again within a few days

Keep Out of Reach of Children

If swallowed, get medical help or contact a Poison Control Center right away.

Directions

- apply as needed

Inactive ingredients

ozokerite, petrolatum, ethylhexyl palmitate, squalane, octyldodecanol, myristyl myristate, ricinus communis (castor) seed oil, myristyl lactate, cetyl alcohol, flavor, myristyl laurate, myristyl alcohol, ammonium glycyrrhizate, BHT, menthol, tocopheryl acetatate [vitamin E]

Questions?

1-877-636-2677 MON-FRI 9 AM to 5 PM (EST)

softlips.com